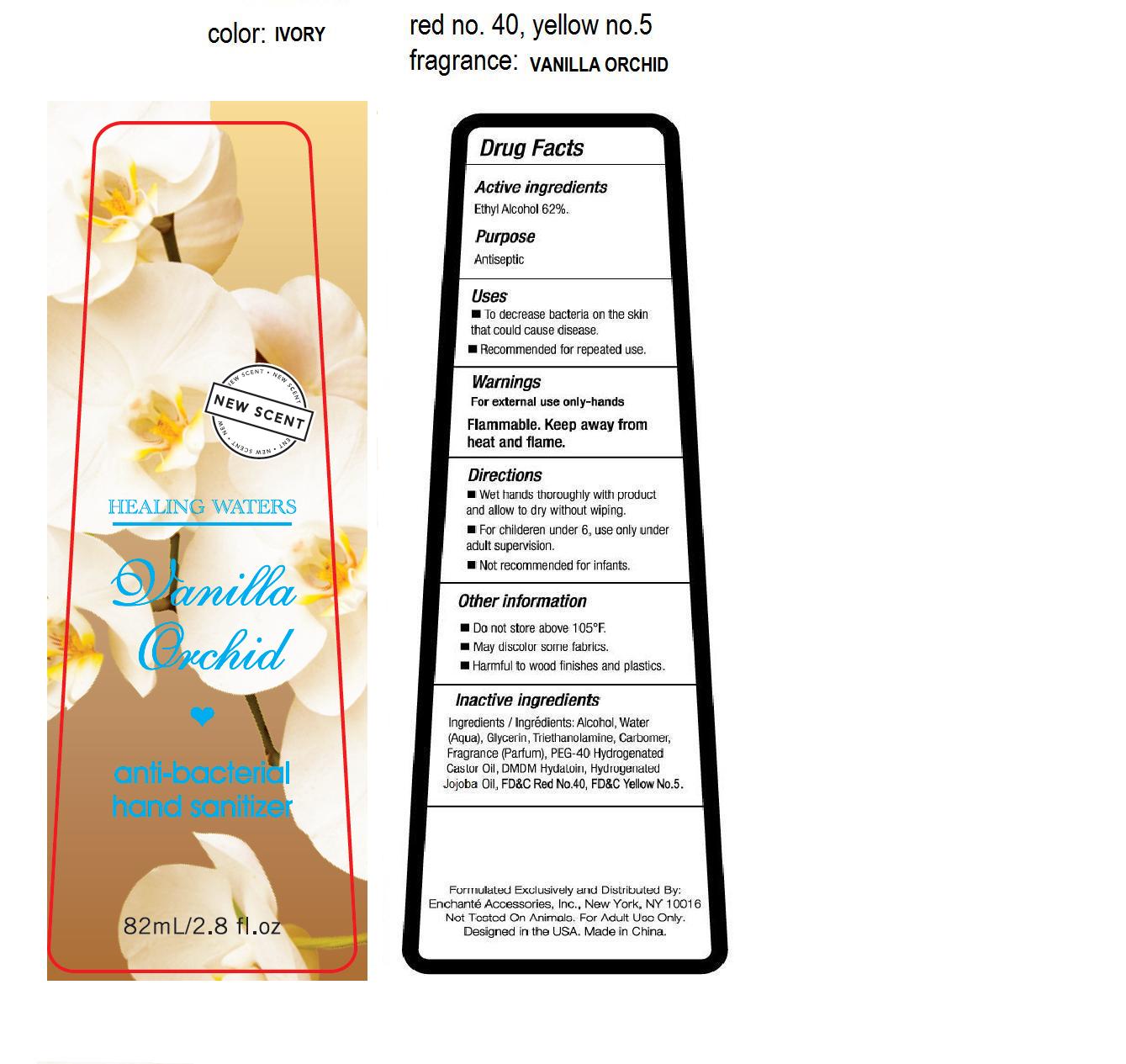 DRUG LABEL: Healing Waters Vanilla Orchid Anti-Bacterial Hand Sanitizer
NDC: 49371-033 | Form: LIQUID
Manufacturer: ALILY (ZHANGZHOU) BATH PRODUCTS LTD.
Category: otc | Type: HUMAN OTC DRUG LABEL
Date: 20100304

ACTIVE INGREDIENTS: ALCOHOL 62 g/100 g
INACTIVE INGREDIENTS: WATER 33.945 g/100 g; GLYCERIN 2 g/100 g; TROLAMINE 0.3 g/100 g; CARBOMER HOMOPOLYMER TYPE A 0.3 g/100 g; POLYOXYL 40 HYDROGENATED CASTOR OIL 0.8 g/100 g; DMDM HYDANTOIN 0.2 g/100 g; FD&C YELLOW NO. 5 0.007 g/100 g; FD&C RED NO. 40 0.003 g/100 g

Drug Fact

Active Ingredient

Ethyl Alcohol 62%

Purpose:

Antiseptic

Uses:

- To decrease bacteria on the skin that could cause diseases

- Recommended for repeated use.

Warnings:

For external use only-hands.

Flammable-keep away from heat and flame

Directions

- Wet hands thoroughly with product and allow to dry without wiping
- For children under 6, use only under adult supervision
- Not recommended for infants

Other Information

- Do not store above 105 F
- May discolor some fabrics
- Harmful to wood finishes and plastics

Inactive Ingredients

Water (aqua), Glycerin, Triethanolamine, Carbomer,Fragrance (Parfume), PEG-40 hydrogenated castor oil, DMDM hydantoin, Hydrogenated Jojoba Oil, FD and C Yellow No. 5, FD and C Red No. 40

PACKAGE LABEL

picture